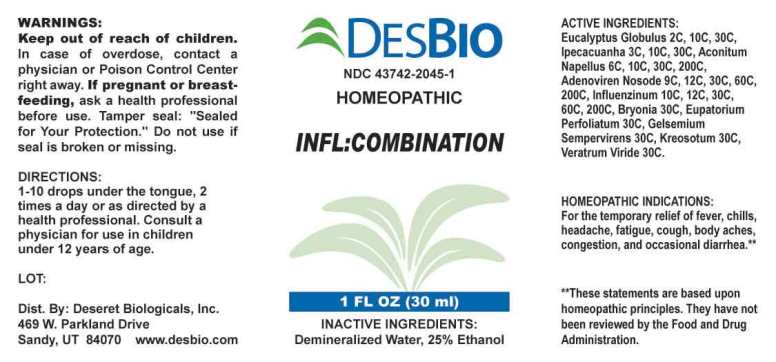 DRUG LABEL: INFL Combination
NDC: 43742-2045 | Form: LIQUID
Manufacturer: Deseret Biologicals, Inc.
Category: homeopathic | Type: HUMAN OTC DRUG LABEL
Date: 20230227

ACTIVE INGREDIENTS: EUCALYPTUS GLOBULUS LEAF 2 [hp_C]/1 mL; IPECAC 3 [hp_C]/1 mL; ACONITUM NAPELLUS WHOLE 6 [hp_C]/1 mL; HUMAN ADENOVIRUS E SEROTYPE 4 STRAIN CL-68578 ANTIGEN 9 [hp_C]/1 mL; INFLUENZA A VIRUS A/VICTORIA/2570/2019 IVR-215 (H1N1) ANTIGEN (FORMALDEHYDE INACTIVATED) 10 [hp_C]/1 mL; INFLUENZA A VIRUS A/TASMANIA/503/2020 IVR-221 (H3N2) ANTIGEN (FORMALDEHYDE INACTIVATED) 10 [hp_C]/1 mL; INFLUENZA B VIRUS B/WASHINGTON/02/2019 ANTIGEN (FORMALDEHYDE INACTIVATED) 10 [hp_C]/1 mL; INFLUENZA B VIRUS B/PHUKET/3073/2013 ANTIGEN (FORMALDEHYDE INACTIVATED) 30 [hp_C]/1 mL; BRYONIA ALBA ROOT 30 [hp_C]/1 mL; EUPATORIUM PERFOLIATUM FLOWERING TOP 30 [hp_C]/1 mL; GELSEMIUM SEMPERVIRENS ROOT 30 [hp_C]/1 mL; WOOD CREOSOTE 30 [hp_C]/1 mL; VERATRUM VIRIDE ROOT 30 [hp_C]/1 mL
INACTIVE INGREDIENTS: WATER; ALCOHOL

DRUG FACTS:

ACTIVE INGREDIENTS:

Eucalyptus Globulus 2C, 10C, 30C, Ipecacuanha 3C, 10C, 30C, Aconitum Napellus 6C, 10C, 30C, 200C, Adenoviren Nosode 9C, 12C, 30C, 60C, 200C, Influenzinum (2021-2022) 10C, 12C, 30C, 60C, 200C, Bryonia (Alba) 30C, Eupatorium Perfoliatum 30C, Gelsemium Sempervirens 30C, Kreosotum 30C, Veratrum Viride 30C.

HOMEOPATHIC INDICATIONS:

For the temporary relief of fever, chills, headache, fatigue, cough, body aches, congestion, and occasional diarrhea.**

**These statements are based upon homeopathic principles. They have not been reviewed by the Food and Drug Administration.

WARNINGS:

Keep out of reach of children. In case of overdose, contact a physician or Poison Control Center right away.
If pregnant or breast-feeding, ask a health professional before use.
Tamper seal: "Sealed for Your Protection." Do not use if seal is broken or missing.

Warning: Severe or persistent sore throat or sore throat accompanied by high fever, headache, nausea, and vomiting may be serious. Consult a physician promptly. Do not use more than two days or administer to children under 3 years of age unless directed by a physician.

Keep out of reach of children. In case of overdose, contact a physician or Poison Control Center right away.

DIRECTIONS:

1-10 drops under the tongue, 2 times a day or as directed by a health professional. Consult a physician for use in children under 12 years of age.

HOMEOPATHIC INDICATIONS:

For the temporary relief of fever, chills, headache, fatigue, cough, body aches, congestion, and occasional diarrhea.**

**These statements are based upon homeopathic principles. They have not been reviewed by the Food and Drug Administration.

INACTIVE INGREDIENTS:

Demineralized Water, 25% Ethanol

QUESTIONS:

Dist. By: Deseret Biologicals, Inc.
469 W. Parkland Drive
Sandy, UT 84070 www.desbio.com

PACKAGE LABEL DISPLAY:

DESBIO
NDC 43742-2045-1
HOMEOPATHIC
INFL:COMBINATION
1 FL OZ (30 ml)